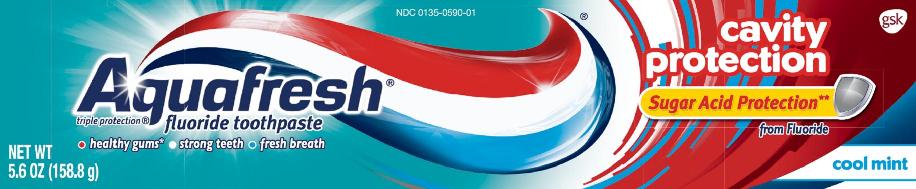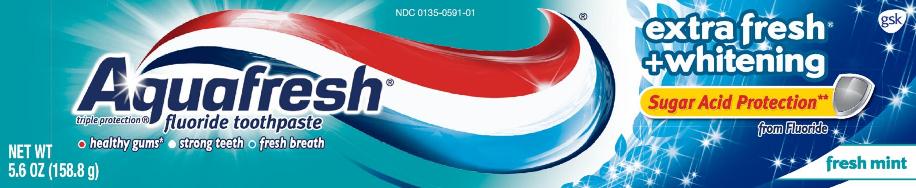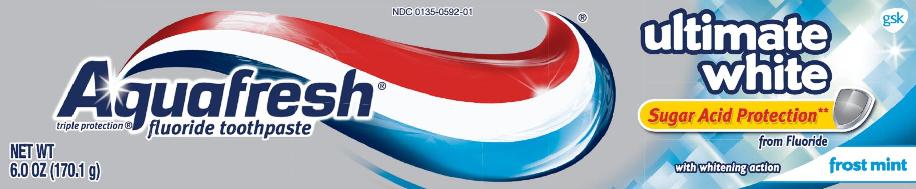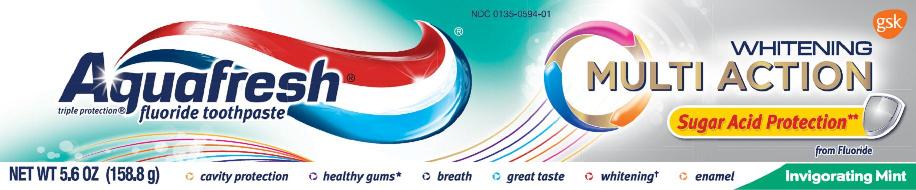 DRUG LABEL: AQUAFRESH

NDC: 0135-0590 | Form: PASTE
Manufacturer: Haleon US Holdings LLC
Category: otc | Type: HUMAN OTC DRUG LABEL
Date: 20260216

ACTIVE INGREDIENTS: SODIUM FLUORIDE 1.15 mg/1 g
INACTIVE INGREDIENTS: WATER; HYDRATED SILICA; SORBITOL; GLYCERIN; SODIUM LAURYL SULFATE; XANTHAN GUM; TITANIUM DIOXIDE; POLYETHYLENE GLYCOL 400; SACCHARIN SODIUM; CARRAGEENAN; D&C RED NO. 30; FD&C BLUE NO. 1

Drug Facts

Active ingredient (Cavity Protection, Extra Fresh +Whitening, Multi Action Whitening)

Sodium fluoride 0.25% (0.15% w/v fluoride ion)

Active ingredient(ultimate white)

Sodium fluoride 0.24% (0.15% w/v fluoride ion)

Purpose

Anticavity

Use

aids in the prevention of dental cavities

Warnings

When using this product,

if irritation occurs discontinue use

Keep out of reach of children under 6 years of age.

If more than used for brushing is accidentally swallowed, get medical help or contact a Poison Control Center right away.

Directions

- adults and children 2 years and older:
  - apply toothpaste onto a toothbrush
  - brush teeth thoroughly, preferably after each meal, or at least twice a day, and not more than 3 times a day, or as directed by a dentist or doctor. Minimize swallowing. Spit out after brushing.
  - to minimize swallowing for children under 6 years of age, use a pea-sized amount and supervise brushing and rinsing until good habits are established.
- children under 2 years of age:Consult a dentist or doctor

Other information

- store below 30°C (86°F)

Inactive ingredients (Cavity Protection)

water, hydrated silica, sorbitol, glycerin, sodium lauryl sulfate, xanthan gum, flavor, titanium dioxide, PEG-8, sodium saccharin, carrageenan, red 30, blue 1

Inactive ingredients (Extra Fresh +Whitening)

water, hydrated silica, sorbitol, glycerin, sodium lauryl sulfate, flavor, xanthan gum, titanium dioxide, PEG-8, sodium saccharin, carrageenan, red 30, blue 1

Inactive ingredients (Multi Action Whitening)

water, hydrated silica, sorbitol, glycerin, PEG-8, sodium lauryl sulfate, xanthan gum, flavor, titanium dioxide, cocamidopropyl betaine, sodium citrate, sodium saccharin, zinc chloride, red 30, blue 1

Inactive ingredients (ultimate white)

water, hydrated silica, sorbitol, glycerin, pentasodium triphosphate, PEG-8, sodium lauryl sulfate, titanium dioxide, flavor, xanthan gum, sodium hydroxide, sodium saccharin, red 30, blue 1

Questions or comments?

Call toll-free 1-800-897-5623

Principal Display Panel

NDC 0135-0590-01

- Aquafresh®

fluoride toothpaste

triple protection®

- healthy gums*
- strong teeth
- fresh breath

cavity protection

Sugar Acid Protection**

from Fluoride

cool mint

NET WT 5.6 OZ (158.8 g)

**With Sugar Acid Protection provided by fluoride, which strengthens enamel, creating a shield that protects the tooth surface against sugar acid attack.

*with twice daily brushing

ALWAYS FOLLOW THE LABEL

Trademarks are owned by or licensed to the GSK group of companies.

©2015 GSK group of companies or its licensor. All rights reserved.

GSKConsumer Healthcare

Warren, NJ 07059

Made in Taiwan

1-800-897-5623

105263XA

Principal Display Panel

NDC 0135-0591-01

- Aquafresh®

fluoride toothpaste

triple protection®

- healthy gums*
- strong teeth
- fresh breath

extra fresh +whitening

Sugar Acid Protection**

from Fluoride

fresh mint

NET WT 5.6 OZ (158.8 g)

**With Sugar Acid Protection provided by fluoride, which strengthens enamel, creating a shield that protects the tooth surface against sugar acid attack.

*with twice daily brushing

ALWAYS FOLLOW THE LABEL

Trademarks are owned by or licensed to the GSK group of companies.

©2015 GSK group of companies or its licensor. All rights reserved.

GSKConsumer Healthcare

Warren, NJ 07059

1-800-897-5623

105282XA

Principal Display Panel

NDC 0135-0594-01

- Aquafresh®

fluoride toothpaste

triple protection®

WHITENING

MULTI ACTION

Sugar Acid Protection**

from Fluoride

NET WT 5.6 OZ (158.8 g)

cavity protection

healthy gums*

breath

great taste

whitening†

enamel

Invigorating Mint

cavity protection

healthy gums*

fresh breath

great taste

removes surface stains

enamel strengthening

**With Sugar Acid Protection provided by fluoride, which strengthens enamel, creating a shidl that protects the tooth surface against sugar acid attack.

*with twice daily brushing

†whitens by removing surface stains

ALWAYS FOLLOW THE LABEL

Trademarks are owned by or licensed to the GSK group of companies.

©2015 GSK group of companies or its licensor. All rights reserved.

GSKConsumer Healthcare

Warren, NJ 07059

105384XA

Principal Display Panel

NDC 0135-0592-01

- Aquafresh®

fluoride toothpaste

triple protection®

ultimate white

Sugar Acid Protection**

from Fluoride

with whitening action

frost mint

NET WT6.0 OZ (170.1 g)

- Aquafresh®Ultimate White toothpaste gently polishes your teeth, lifts away stains and helps to prevent new stains appearing.
- **With Sugar Acid Protection provided by fluoride, which strengthens enamel, creating a shield that protects the tooth surface against sugar acid attach.

- healthy gums†
- strong teeth
- fresh breath
- †with twice daily brushing

ALWAYS FOLLOW THE LABEL

Trademarks are owned by or licensed to the GSK group of companies.

©2015 GSK group of companies or its licensor. All rights reserved.

GSKConsumer Healthcare, Warren, NJ 07059

1-800-897-5623

105287XA